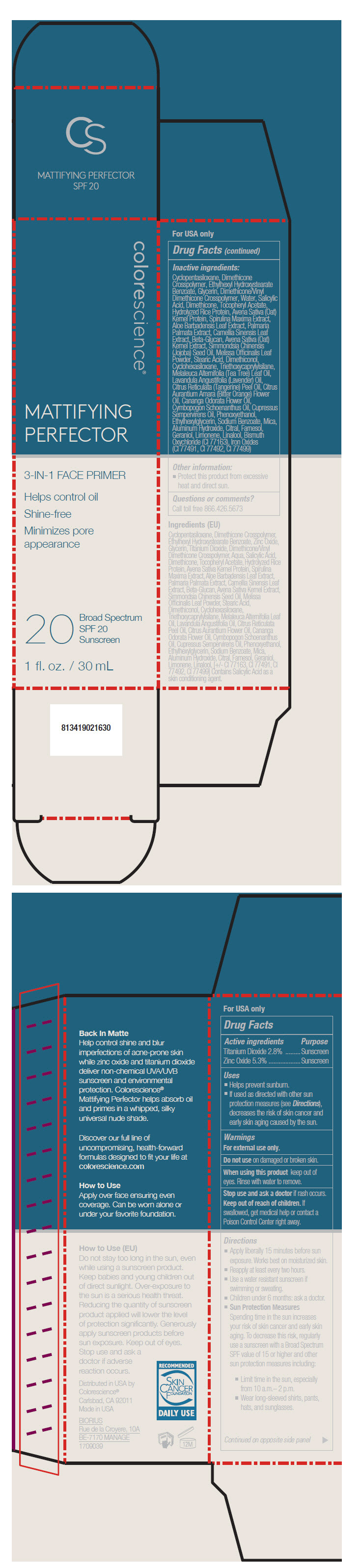 DRUG LABEL: Mattifying Perfector SPF 20 Sunscreen
NDC: 68078-018 | Form: LIQUID
Manufacturer: Colorescience
Category: otc | Type: HUMAN OTC DRUG LABEL
Date: 20181106

ACTIVE INGREDIENTS: Titanium Dioxide 28 mg/1 mL; Zinc Oxide 53 mg/1 mL
INACTIVE INGREDIENTS: Cyclomethicone 5; DIMETHICONE CROSSPOLYMER (450000 MPA.S AT 12% IN CYCLOPENTASILOXANE); Ethylhexyl Hydroxystearate Benzoate; Glycerin; DIMETHICONE/VINYL DIMETHICONE CROSSPOLYMER (SOFT PARTICLE); Water; Salicylic Acid; Dimethicone; .Alpha.-Tocopherol Acetate; RICE BRAN; Oat; ARTHROSPIRA MAXIMA; ALOE VERA LEAF; DULSE; GREEN TEA LEAF; POLYSACCHARIDE-K; JOJOBA OIL; MELISSA OFFICINALIS LEAF; Stearic Acid; DIMETHICONOL (100000 CST); CYCLOMETHICONE 6; Triethoxycaprylylsilane; TEA TREE OIL; LAVENDER OIL; MANDARIN OIL; CITRUS AURANTIUM FLOWER OIL; CANANGA OIL; Cymbopogon Schoenanthus Oil; CUPRESSUS SEMPERVIRENS LEAF OIL; Phenoxyethanol; ETHYLHEXYLGLYCERIN; Sodium Benzoate; Mica; Aluminum Hydroxide; Citral; Farnesol; Geraniol; Limonene, (+)-; BISMUTH OXYCHLORIDE; FERRIC OXIDE YELLOW; FERRIC OXIDE RED; FERROSOFERRIC OXIDE

Mattifying Perfector SPF 20 Sunscreen

Drug Facts

ACTIVE INGREDIENT

Active ingredients | Purpose
Titanium Dioxide 2.8% | Sunscreen
Zinc Oxide 5.3% | Sunscreen

Uses

- Helps prevent sunburn.
- If used as directed with other sun protection measures (see Directions), decreases the risk of skin cancer and early skin aging caused by the sun.

Warnings

For external use only.

Do not use on damaged or broken skin.

When using this product keep out of eyes. Rinse with water to remove.

Stop use and ask a doctor if rash occurs.

Keep out of reach of children. If swallowed, get medical help or contact a Poison Control Center right away.

Directions

- Apply liberally 15 minutes before sun exposure. Works best on moisturized skin.
- Reapply at least every two hours.
- Use a water resistant sunscreen if swimming or sweating.
- Children under 6 months: ask a doctor.
- Sun Protection Measures
  Spending time in the sun increases your risk of skin cancer and early skin aging. To decrease this risk, regularly use a sunscreen with a Broad Spectrum SPF value of 15 or higher and other sun protection measures including:
  - Limit time in the sun, especially from 10 a.m.– 2 p.m.
  - Wear long-sleeved shirts, pants, hats, and sunglasses.

Inactive ingredients

Cyclopentasiloxane, Dimethicone Crosspolymer, Ethylhexyl Hydroxystearate Benzoate, Glycerin, Dimethicone/Vinyl Dimethicone Crosspolymer, Water, Salicylic Acid, Dimethicone, Tocopheryl Acetate, Hydrolyzed Rice Protein, Avena Sativa (Oat) Kernel Protein, Spirulina Maxima Extract, Aloe Barbadensis Leaf Extract, Palmaria Palmata Extract, Camellia Sinensis Leaf Extract, Beta-Glucan, Avena Sativa (Oat) Kernel Extract, Simmondsia Chinensis (Jojoba) Seed Oil, Melissa Officinalis Leaf Powder, Stearic Acid, Dimethiconol, Cyclohexasiloxane, Triethoxycaprylylsilane, Melaleuca Alternifolia (Tea Tree) Leaf Oil, Lavandula Angustifolia (Lavender) Oil, Citrus Reticulata (Tangerine) Peel Oil, Citrus Aurantium Amara (Bitter Orange) Flower Oil, Cananga Odorata Flower Oil, Cymbopogon Schoenanthus Oil, Cupressus Sempervirens Oil, Phenoxyethanol, Ethylhexylglycerin, Sodium Benzoate, Mica, Aluminum Hydroxide, Citral, Farnesol, Geraniol, Limonene, Linalool, Bismuth Oxychloride (CI 77163), Iron Oxides (CI 77491, CI 77492, CI 77499)

Other information

- Protect this product from excessive heat and direct sun.

Questions or comments?

Call toll free 866.426.5673

Distributed in USA by
Colorescience®
Carlsbad, CA 92011

PRINCIPAL DISPLAY PANEL - 30 mL Tube Carton

colorescience®

MATTIFYING
PERFECTOR

3-IN-1 FACE PRIMER

Helps control oil

Shine-free

Minimizes pore
appearance

20
Broad Spectrum
SPF 20
Sunscreen

1 fl. oz. / 30 mL